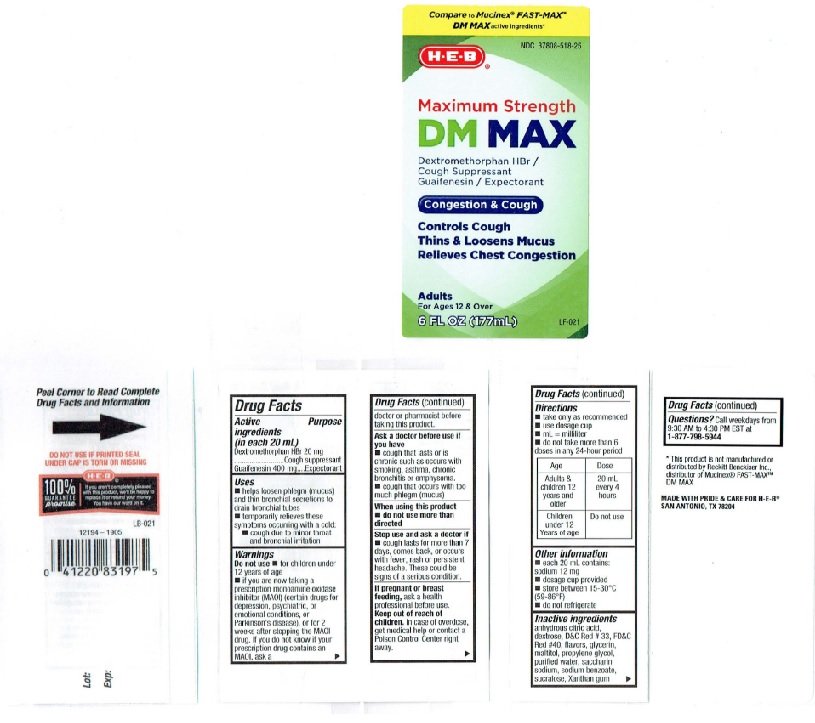 DRUG LABEL: Maximum Strength DM MAX
NDC: 37808-518 | Form: LIQUID
Manufacturer: H E B
Category: otc | Type: HUMAN OTC DRUG LABEL
Date: 20231229

ACTIVE INGREDIENTS: DEXTROMETHORPHAN HYDROBROMIDE 20 mg/20 mL; GUAIFENESIN 400 mg/20 mL
INACTIVE INGREDIENTS: ANHYDROUS CITRIC ACID; DEXTROSE; D&C RED NO. 33; FD&C RED NO. 40; GLYCERIN; MALTITOL; PROPYLENE GLYCOL; WATER; SACCHARIN SODIUM; SODIUM BENZOATE; SUCRALOSE; XANTHAN GUM

H E B Maximum Strength DM MAX

Drug Facts

Active ingredients (in each 20 mL)
Dextromethorphan HBr 20 mg
Guaifenesin 400 mg

Purpose

Dextromethorphan HBr ... Cough suppressant
Guaifenesin ....................Expectorant

Uses
• helps loosen phlegm (mucus)
and thin bronchial secretions to
drain bronchial tubes
• temporarily relieves these
symploms occurring with a cold:
• cough due to minor throat and
bronchial irritation

Warnings
Do not use • for children under
12 years of age
• if you are now taking a
prescription monoamine oxiclase
inhibitor (MAOI) (certain drugs for
depression. psychiatric.
or emotional conditions, or
Parkinson's disease), or
for 2 weeks after stopping the MAOI
drug. If you do not know if your
prescription drug contains an
MAOI, ask a doctor or pharmacist
before taking this product.

Ask a doctor before use if
you have
• cough that lasts or is chronic
such as occurs with smoking,
asthma, chronic bronchitis or
emphysema.
• cough that occurs with too
much phlegm (mucus)

When using this product
• do not use more than
directed

Slop use and ask a doctor if
• cough lasts for more than 7
days, comes back, or occurs
with fever, rash or persistent
headache. These could be
signs of a serious condition.

If pregnant or breast
feeding, ask a health
professional before use.

Keep out of reach of
children. In case of overdose,
get medical help or contact a
Poison Control Center right
away.

Directions
• take only as recommended
• use dosage cup
• mL = milliliter
• do not take more than 6
doses in any 24-hour period

Age Dose

Adults & 20 ml
children 12 every 4
years and hours
older

Children Do not use
under 12
Years of age

Other information
• each 20 mL contains:
sodium 12 mg
• dosage cup provided
• store between 15-30ο C
(59-86ο F)
• do not refrigerate

Inactive ingredients
anhydrous citric acid,
dextrose, D&C Red #33, FD&C
Red #40, flavors, glycerin,
maltitol, propylene glycol,
purified waler, saccharin
sodium, sodium benzoate,
sucralose, Xanthan gum

QUESTIONS

Questions? Call weekdays from 9:30 AM to 4:30 PM EST at
1-877-798-5944

Product Label

Compare to Mucinex® FAST-MAX™

DM MAX active ingredients*

NDC 37808-518-25
H-E-B®

Maximum Strength
DM MAX

Dextromethorphan HBr /
Cough Suppressant
Guaifenesin / Expectorant

Congestion & Cough

Controls Cough
Thins & Loosens Mucus
Relieves Chest Congestion

Adults

For Ages 12 & Over

6 FL OZ (177mL)

LF 021

Peel Corner to Read Complete
Drug Facts and Information →

DO NOT USE IF PRINTED SEAL

UNDER CAP IS TORN OR MISSING

H-E-B®

100%
GUARANTEE
promise

If you aren't completely pleased
with this product, we'll be happy to
replace it or refund your money.
You have our word on it.

LB-021

12194-1905

0 41220 83197 5
Lot:
Exp:

*This product is not manufactured or
distributed by Reekitt Benckiser Inc.,
distributor of Mucinex® FAST-MAXTM
DM MAX

MADE WITH PRIDE & CARE FOR H-E-B®

SAN ANTONIO, TEXAS, 782044

res